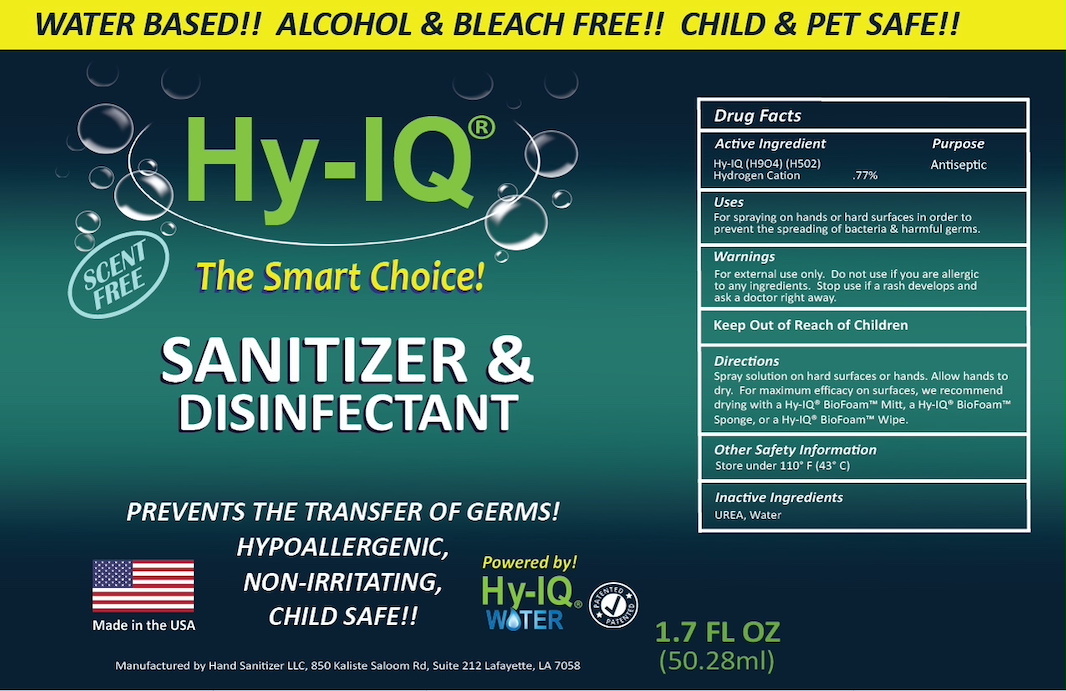 DRUG LABEL: Hy-IQ Sanitizer and Disinfectant
NDC: 76701-360 | Form: SPRAY
Manufacturer: HAND SANITIZER LLC
Category: otc | Type: HUMAN OTC DRUG LABEL
Date: 20210623

ACTIVE INGREDIENTS: HYDROGEN CATION 10 mg/1 mL
INACTIVE INGREDIENTS: UREA 50 mg/1 mL; WATER 940 mg/1 mL

ACTIVE INGREDIENT

Hy- IQ Water ([H9O4] | [H5O2])

Hydrogen Cation .77%

PURPOSE

Antiseptic

INDICATIONS AND USAGE

For spraying on hands or hard surfaces in order to prevent the spreading of bacteria & harmful germs.

WARNINGS

For external use only. Do not use if you are allergic to any ingredients. Stop use if rash develops and ask a doctor right away.

Keep Out of Reach of Children

DOSAGE AND ADMINISTRATION

Spray solution on hard surfaces or hands. Allow hands to dry. For maximum efficacy on surfaces, we recommend drying with a Hy-IQ® Biofoam™ Mitt, a Hy-IQ® Biofoam™ Sponge, or a Hy-IQ® Biofoam™ Wipe.

OTHER SAFETY INFORMATION

Store under 110°F (43C)

INACTIVE INGREDIENT

Water, UREA